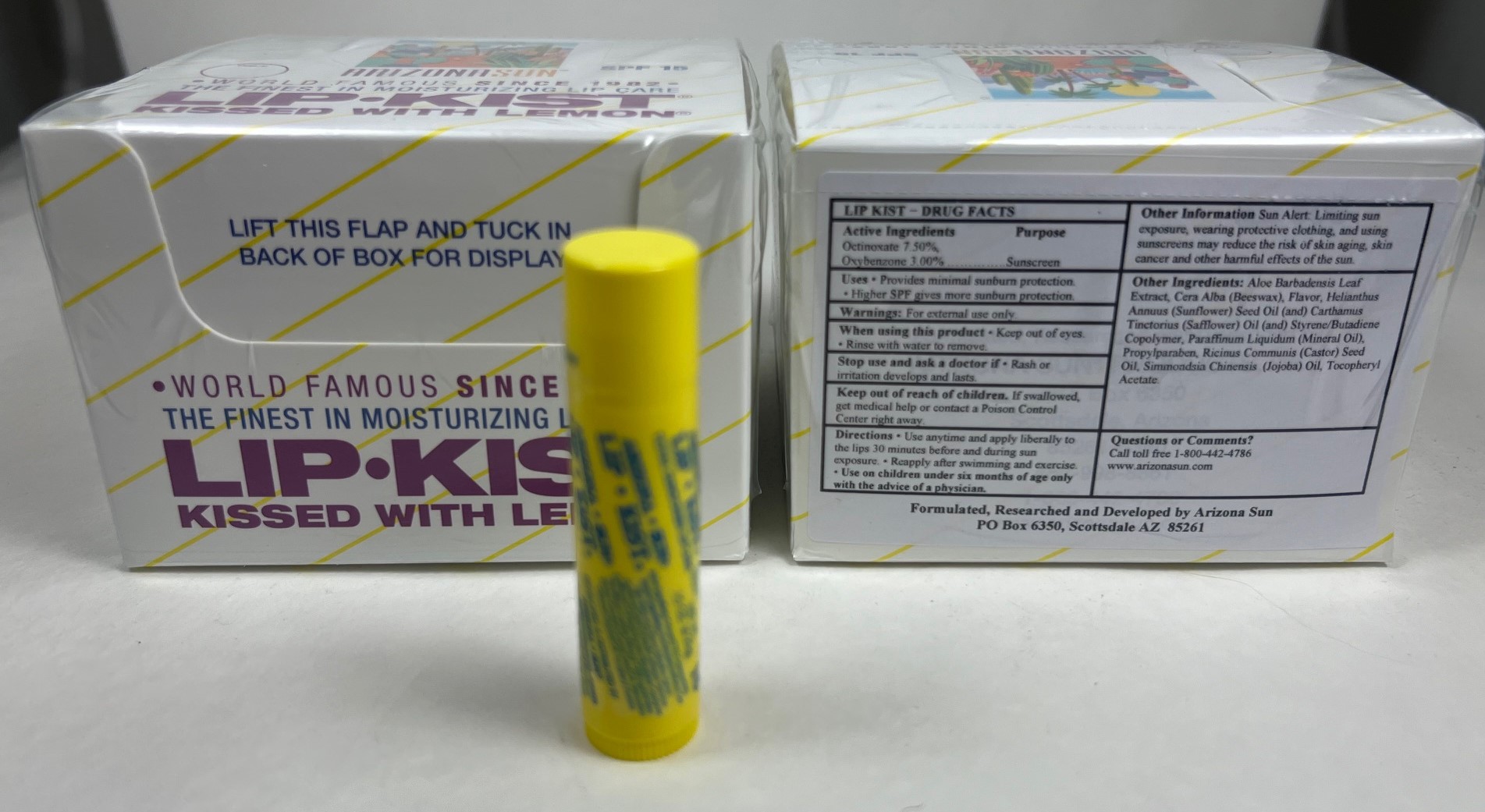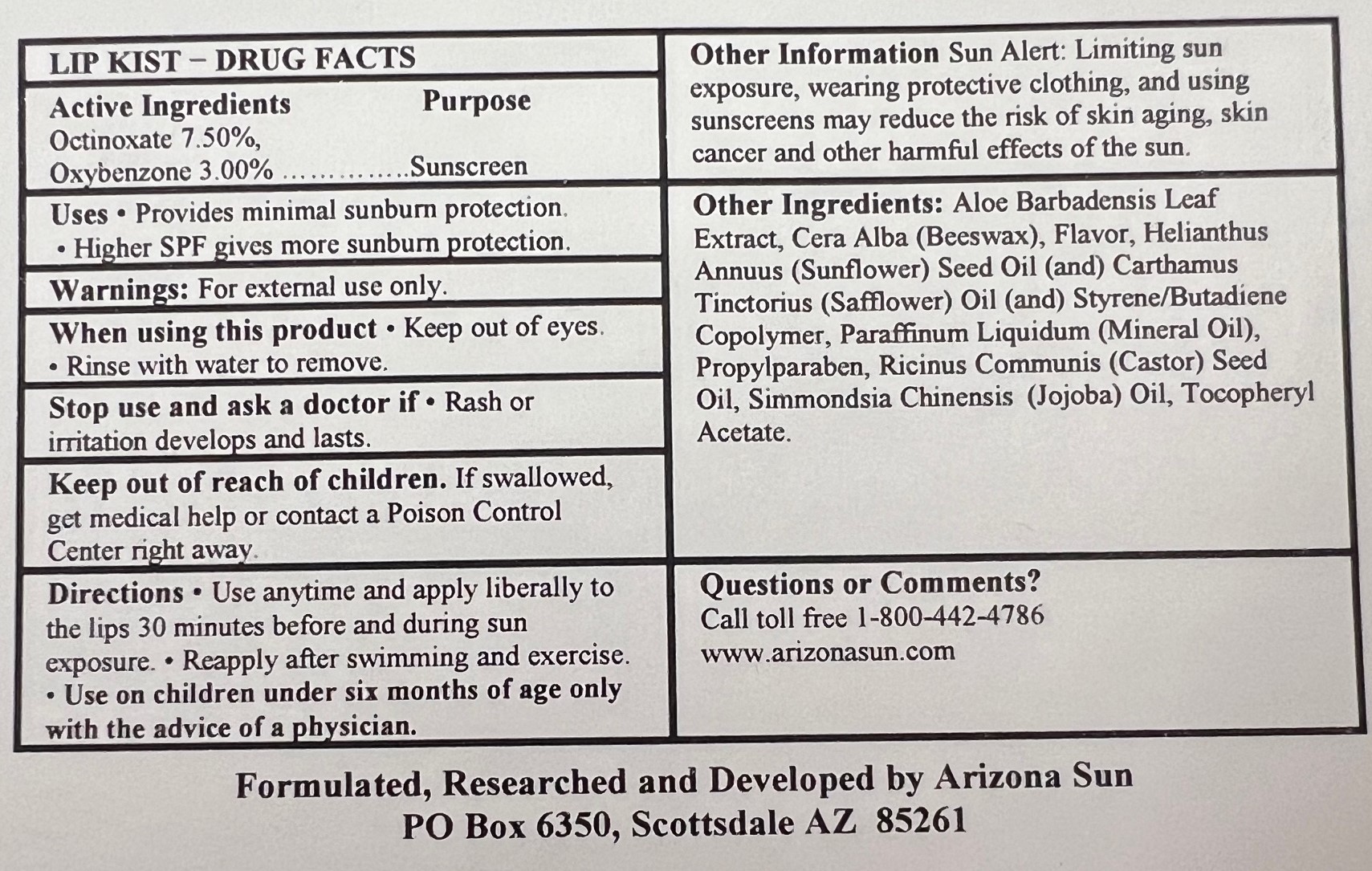 DRUG LABEL: Arizona Sun Products Lipkist Lip Balm SPF 15
NDC: 61973-401 | Form: LIPSTICK
Manufacturer: Arizona Sun Products
Category: otc | Type: HUMAN OTC DRUG LABEL
Date: 20240223

ACTIVE INGREDIENTS: OXYBENZONE 30 mg/1 g; OCTINOXATE 75 mg/1 g
INACTIVE INGREDIENTS: .ALPHA.-TOCOPHEROL ACETATE; PROPYLPARABEN; WHITE WAX; SIMMONDSIA CHINENSIS SEED; MINERAL OIL; SAFFLOWER OIL; CASTOR OIL; ALOE VERA LEAF; SUNFLOWER SEED

Lipkist Lip Balm Box

Active Ingredients

Octinoxate 7.50%, Oxybenzone 3.00%

Purpose

Sunscreen

Uses

Provides mminimal sunburn protection. Higher SPF gives more sunburn protection

Warnings

For external use only.

When using this product

keep out of eyes. Rinse with water to remove.

Stop and ask a doctor

if rash or irritation develops and lasts.

Keep out of the reach of children.

If swallowed get medical help or contact a poison control center right away.

Directions

Use anytime and apply liberally to the lips 30 minutes before and during sun exposure. Reapply after swimming and exercise. Use on children under the age of six months only wih the advise of a physician.

Other Information

Sun Alert: Limiting sun exposure, wearing protective clothing, and using suscreen may reduce the risk of skin aging, skin cancer and other harmful effects of the sun.

Inactive Ingredients

Aloe Barbadensis Leaf (Aloe Vera) Extract, Cera Alba (Beeswax),Flavor, Helianthus Annuus (Sunflower) Seed Oil, Carthamus Tinctorius (Safflower) Seed Oil, Styrene/Butadiene Copolymer, Paraffinum Liquidum, Propylparaben, Ricinus Communis (Castor) Seed Oil, Simmondsia Chinensis (Jojoba) Seed Oil, Tocopheryl Acetate

Questions or Comments?

Call toll free 1-800-442-4786